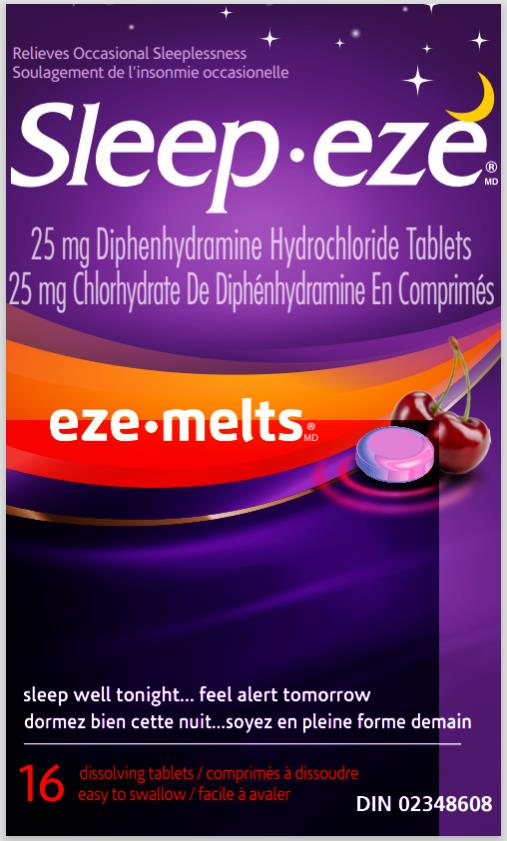 DRUG LABEL: Sleepeze eze melts
NDC: 63029-925 | Form: TABLET
Manufacturer: Medtech Products Inc.
Category: otc | Type: HUMAN OTC DRUG LABEL
Date: 20240118

ACTIVE INGREDIENTS: DIPHENHYDRAMINE HYDROCHLORIDE 25 mg/1 1
INACTIVE INGREDIENTS: CITRIC ACID MONOHYDRATE; CELLULOSE, MICROCRYSTALLINE; ETHYLCELLULOSES; D&C RED NO. 7; HYDROXYPROPYL CELLULOSE, UNSPECIFIED; LACTOSE MONOHYDRATE; MINERAL OIL; MAGNESIUM STEARATE; MANNITOL; STEARIC ACID; POVIDONE; SUCRALOSE; SUCROSE

SleepEze eze melts_Export only 63029-925-16

Drug Facts

Active ingredient (in each tablet)

Diphenhydramine Hydrochloride 25 mg

Purpose

Nighttime sleep aid

Uses

● relieves occasional sleeplessness ● helps to reduce difficulty falling asleep

Warnings

Do not use

●if you are elderly, as this drug may cause excitation rather than sedation ●with any other product containing diphenhydramine, even one used on skin ●in children under 12 years of age

Ask a doctor or pharmacist before use if you

●have ▪a breathing problem such as emphysema or chronic bronchitis ▪glaucoma ▪difficulty urinating ●take sedatives or tranquilizers ●are pregnant or breastfeeding

When using this product

avoid drinking alcohol.

Stop use and ask a doctor if

sleeplessness continues for more than 2 weeks. Sleeplessness may be a symptom of a serious underlying medical illness.

Keep out of reach of children.

In case of overdose, call a poison control centre or get medical help right away

Directions

●Adults and children 12 years and over: ▪take 1 or 2 tablets at bedtime if needed, or as directed by a doctor ▪if you feel drowsy in the morning, reduce dose to 1 tablet

▪do not take more than directed

Other information

▪ Store at 20° to 25°C

Inactive ingredients

citric acid, d&c red 7 lake, ethylcellulose, flavour, hydroxypropyl cellulose, magnesium stearate, mannitol, microcrystalline cellulose, povidone, stearic acid, sucralose, sucrose

Questions?

1-800-443-4908

PRINCIPAL DISPLAY PANEL

Sleep.eze
25 mg Diphenhydramine Hydrochloride Tablets
16 dissolving tablets